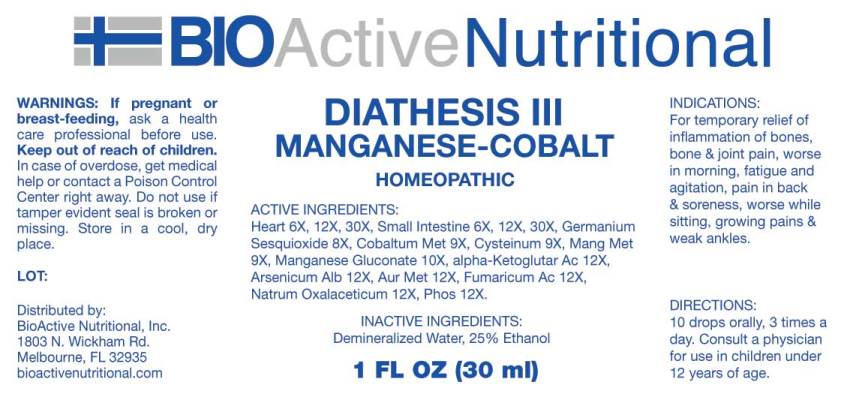 DRUG LABEL: Diathesis
NDC: 43857-0148 | Form: LIQUID
Manufacturer: BioActive Nutritional, Inc.
Category: homeopathic | Type: HUMAN OTC DRUG LABEL
Date: 20171017

ACTIVE INGREDIENTS: PORK HEART 6 [hp_X]/1 mL; PORK INTESTINE 6 [hp_X]/1 mL; GERMANIUM SESQUIOXIDE 8 [hp_X]/1 mL; COBALT 9 [hp_X]/1 mL; CYSTEINE 9 [hp_X]/1 mL; MANGANESE 9 [hp_X]/1 mL; MANGANESE GLUCONATE 10 [hp_X]/1 mL; .ALPHA.-KETOGLUTARIC ACID 12 [hp_X]/1 mL; ARSENIC TRIOXIDE 12 [hp_X]/1 mL; GOLD 12 [hp_X]/1 mL; FUMARIC ACID 12 [hp_X]/1 mL; SODIUM DIETHYL OXALACETATE 12 [hp_X]/1 mL; PHOSPHORUS 12 [hp_X]/1 mL
INACTIVE INGREDIENTS: WATER; ALCOHOL

Drug Facts:

ACTIVE INGREDIENTS:

Heart (Suis) 6X, 12X, 30X, Small Intestine (Suis) 6X, 12X, 30X, Germanium Sesquioxide 8X, Cobaltum Metallicum 9X, Cysteinum 9X, Manganum Metallicum 9X, Manganese Gluconate 10X, alpha-Ketoglutaricum Acidum 12X, Arsenicum Album 12X, Aurum Metallicum 12X, Fumaricum Acidum 12X, Natrum Oxalaceticum 12X, Phosphorus 12X.

INDICATIONS:

For temporary relief of inflammation of bones, bone & joint pain, worse in morning, fatigue and agitation, pain in back & soreness, worse while sitting, growing pains & weak ankles.

WARNINGS:

If pregnant or breast-feeding, ask a health care professional before use.

Keep out of reach of children. In case of overdose, get medical help or contact a Poison Control Center right away.

Do not use if tamper evident seal is broken or missing.

Store in cool, dry place.

DIRECTIONS:

10 drops orally, 3 times a day. Consult a physician for use in children under 12 years of age.

INACTIVE INGREDIENTS:

Demineralized Water, 25% Ethanol.

Keep out of reach of children. In case of overdose, get medical help or contact a Poison Control Center right away.

INDICATIONS:

For temporary relief of inflammation of bones, bone & joint pain, worse in morning, fatigue and agitation, pain in back & soreness, worse while sitting, growing pains & weak ankles.

QUESTIONS:

Distributed by:
BioActive Nutritional, Inc.
1803 N. Wickham Rd.
Melbourne, FL 32935
bioactivenutritional.com

PACKAGE LABEL DISPLAY:

BIOActive Nutritional

DIATHESIS III

HOMEOPATHIC

1 FL OZ (30 ml)